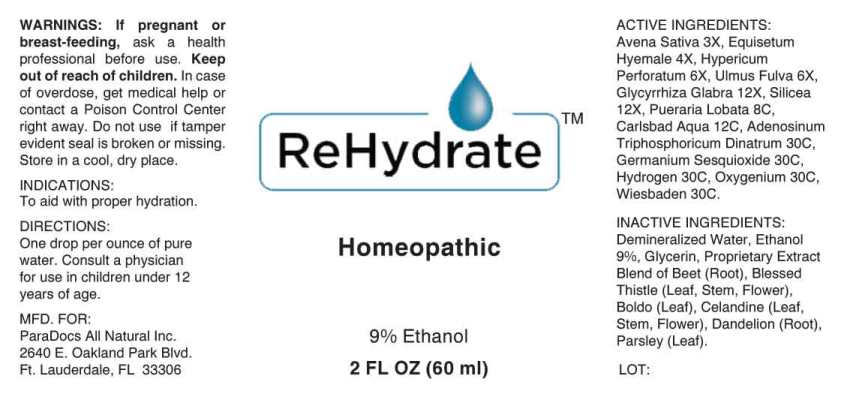 DRUG LABEL: Rehydrate
NDC: 54638-0003 | Form: LIQUID
Manufacturer: ParaDocs All Natural, Inc.
Category: homeopathic | Type: HUMAN OTC DRUG LABEL
Date: 20230110

ACTIVE INGREDIENTS: AVENA SATIVA FLOWERING TOP 3 [hp_X]/1 mL; EQUISETUM HYEMALE 4 [hp_X]/1 mL; HYPERICUM PERFORATUM 6 [hp_X]/1 mL; ULMUS RUBRA BARK 6 [hp_X]/1 mL; GLYCYRRHIZA GLABRA 12 [hp_X]/1 mL; SILICON DIOXIDE 12 [hp_X]/1 mL; PUERARIA MONTANA VAR. LOBATA ROOT 8 [hp_C]/1 mL; WATER 12 [hp_C]/1 mL; ADENOSINE TRIPHOSPHATE DISODIUM 30 [hp_C]/1 mL; GERMANIUM SESQUIOXIDE 30 [hp_C]/1 mL; HYDROGEN 30 [hp_C]/1 mL; OXYGEN 30 [hp_C]/1 mL
INACTIVE INGREDIENTS: ALCOHOL; GLYCERIN; BEET; CENTAUREA BENEDICTA FLOWERING TOP; PEUMUS BOLDUS LEAF; TARAXACUM OFFICINALE ROOT; PARSLEY; CHELIDONIUM MAJUS

Drug Facts:

ACTIVE INGREDIENTS:

Avena Sativa 3X, Equisetum Hyemale 4X, Hypericum Perforatum 6X, Ulmus Fulva 6X, Glycyrrhiza Glabra 12X, Silicea 12X, Pueraria Lobata 8C, Carlsbad Aqua 12C, Adenosinum Triphosphoricum Dinatrum 30C, Germanium Sesquioxide 30C, Hydrogen 30C, Oxygen 30C, Wiesbaden 30C.

INDICATIONS:

To aid with proper hydration.

WARNINGS:

If pregnant or breast-feeding, ask a health professional before use.

Keep out of reach of children. In case of overdose, get medical help or contact a Poison Control Center right away.

Do not use if tamper evident seal is broken or missing.

Store in a cool, dry place.

Keep out of reach of children. In case of overdose, get medical help or contact a Poison Control Center right away.

DIRECTIONS:

One drop per ounce of pure water. Consult a physician for use in children under 12 years of age.

INDICATIONS:

To aid with proper hydration.

INACTIVE INGREDIENTS:

Demineralized Water, Ethanol 9%, Glycerin, Propriety Extract blend of Beet (Root), Blessed Thistle (Leaf, Stem, Flower), Boldo (Leaf), Celandine (Leaf, Stem, Flower), Dandelion (Root), Parsley (Leaf)

QUESTIONS:

MFD. FOR:

ParaDocs All Natural Inc.

2640 E. Oakland Park Blvd.

Ft. Lauderdale, FL 33306

PACKAGE LABEL DISPLAY:

ReHydrate

Homeopathic

2 FL OZ (60 ml)